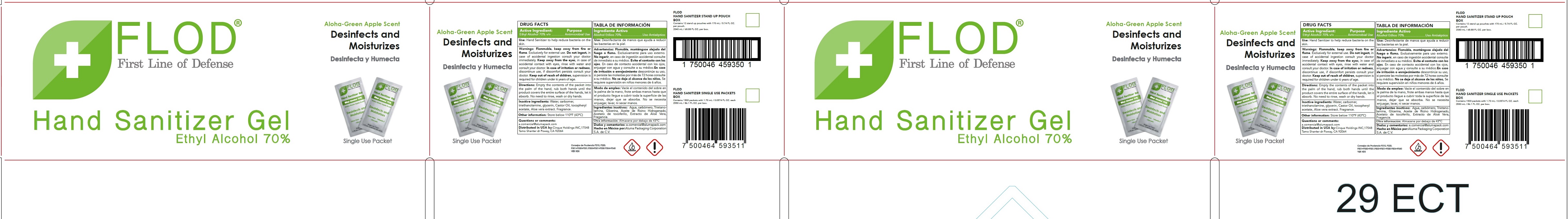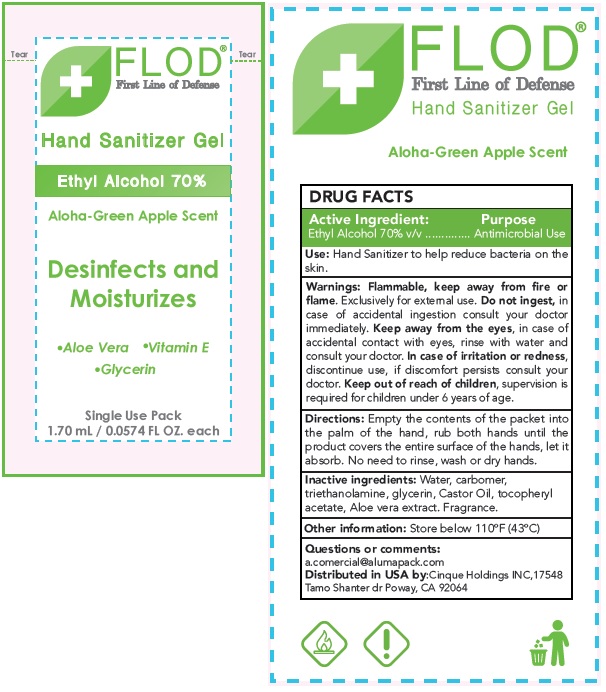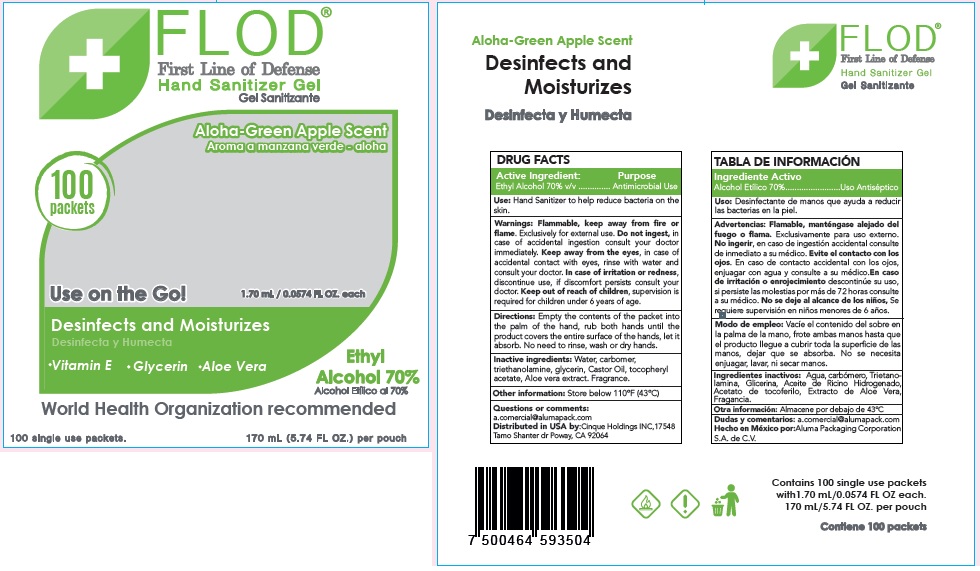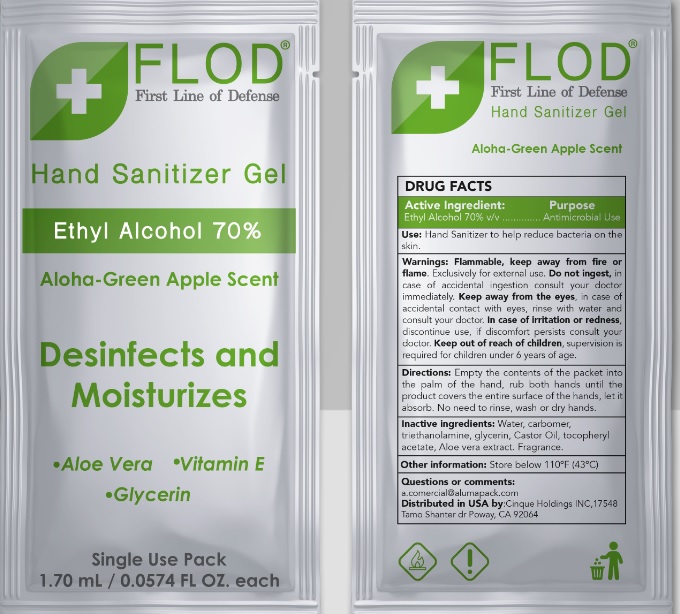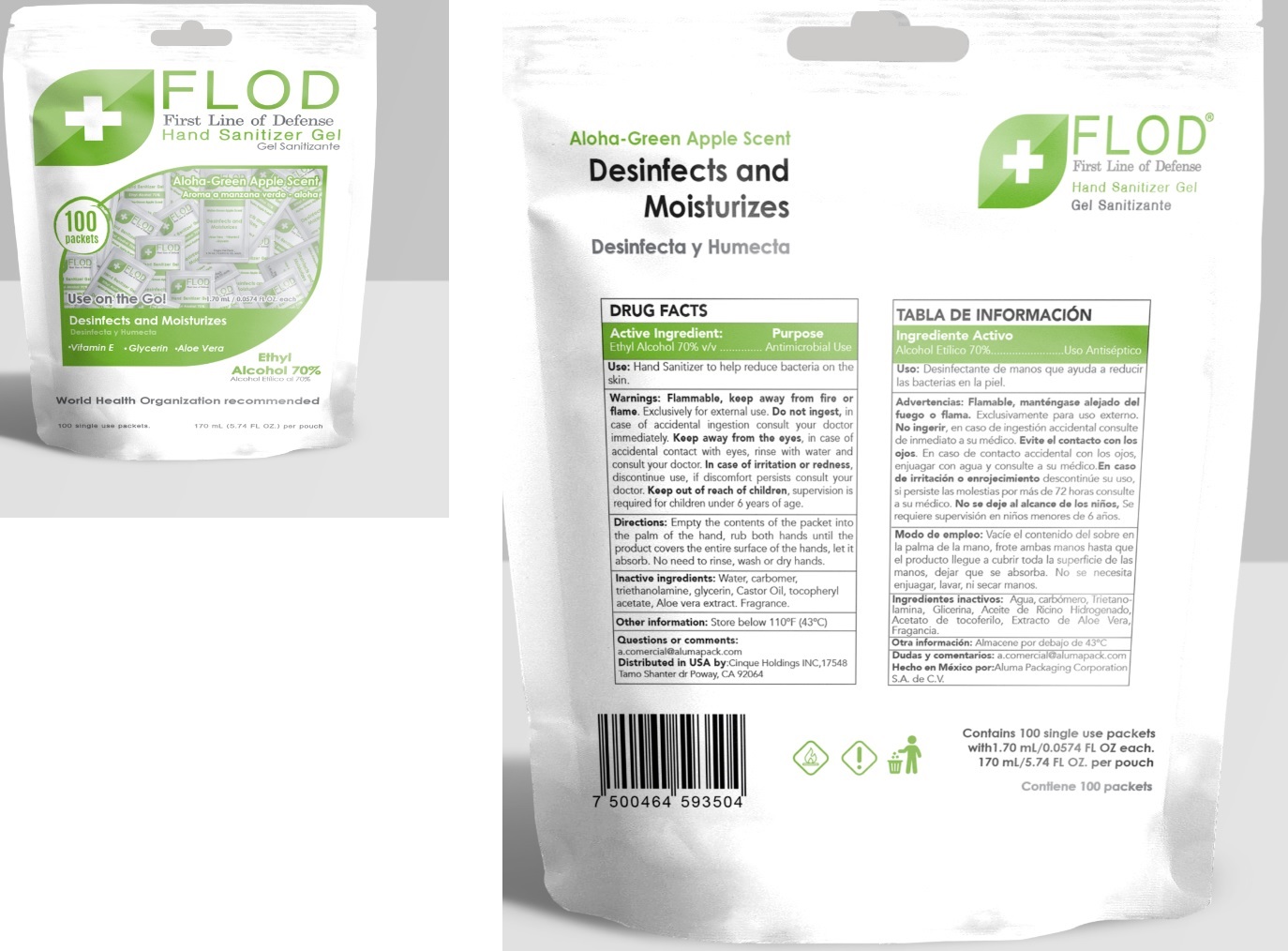 DRUG LABEL: Flod Hand Sanitizer Gel, Aloha-Green Apple Scent
NDC: 81998-001 | Form: GEL
Manufacturer: Aluma Packaging Corporation, S.A. de C.V.
Category: otc | Type: HUMAN OTC DRUG LABEL
Date: 20220309

ACTIVE INGREDIENTS: ALCOHOL 70 mL/100 mL
INACTIVE INGREDIENTS: WATER; CARBOMER HOMOPOLYMER, UNSPECIFIED TYPE; TROLAMINE; GLYCERIN; CASTOR OIL; .ALPHA.-TOCOPHEROL ACETATE; ALOE VERA LEAF

Flod Hand Sanitizer Gel, Aloha-Green Apple Scent

Active Ingredient:

Ethyl Alcohol 70% v/v

Purpose

Antimicrobial Use

Use:

Hand Sanitizer to help reduce bacteria on the skin.

Warnings:

Flammable, keep away from fire or flame. Exclusively for external use. Do not ingest, in case of accidental ingestion consult your doctor immediately. Keep away from the eyes, in case of accidental contact with eyes, rinse with water and consult your doctor. In case of irritation or redness, discontinue use, if discomfort persists consult your doctor.

Keep out of reach of children,

supervision is required for children under 6 years of age.

Directions:

Empty the contents of the packet into the palm of the hand, rub both hands until the product covers the entire surface of the hands, let it
absorb. No need to rinse, wash or dry hands.

Inactive ingredients:

Water, carbomer, triethanolamine, glycerin, Castor Oil, tocopheryl acetate, Aloe vera extract. Fragrance.

Other information:

Store below 110ºF (43ºC)

Questions or comments:

a.comercial@alumpack.com